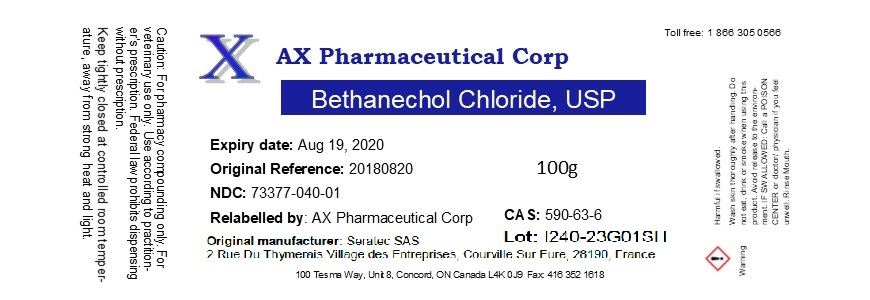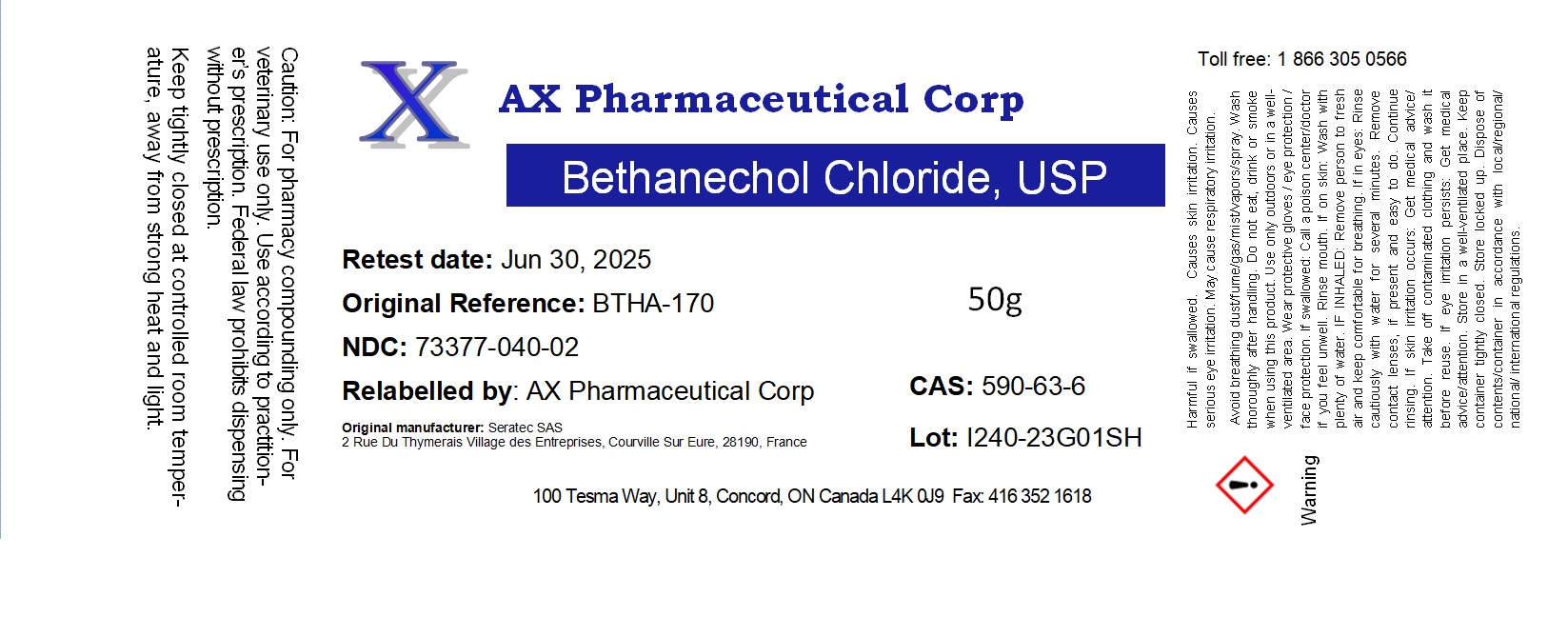 DRUG LABEL: Bethanechol Chloride
NDC: 73377-040 | Form: POWDER
Manufacturer: AX Pharmaceutical Corp
Category: other | Type: BULK INGREDIENT - ANIMAL DRUG
Date: 20231116

ACTIVE INGREDIENTS: BETHANECHOL CHLORIDE 1 g/1 g

Bethanechol Chloride